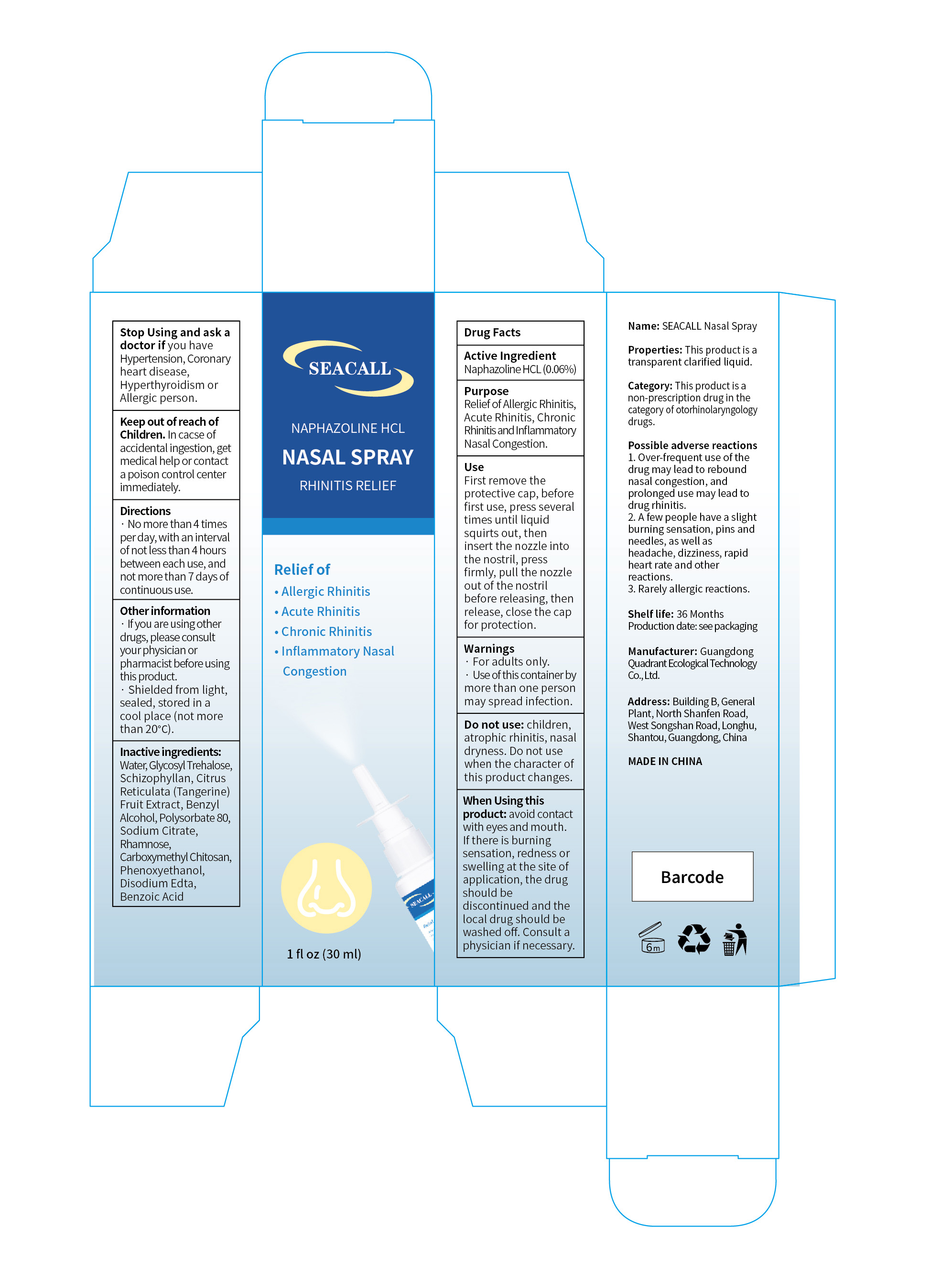 DRUG LABEL: Seacall Nasal Spray.
NDC: 76986-001 | Form: SPRAY
Manufacturer: Guangdong Quadrant Ecological Technology Co., Ltd.
Category: otc | Type: HUMAN OTC DRUG LABEL
Date: 20260123

ACTIVE INGREDIENTS: NAPHAZOLINE HCL 0.06 g/100 mL
INACTIVE INGREDIENTS: EDETATE DISODIUM; SODIUM CITRATE; BENZYL ALCOHOL; N-CARBOXYMETHYLCHITOSAN; SIZOFIRAN; POLYSORBATE 80; RHAMNOSE; PHENOXYETHANOL; WATER; TANGERINE; BENZOIC ACID; GLUCOSYL TREHALOSE

76986-001 Seacall Nasal Spray.

Active Ingredient

Naphazoline HCL (0.06%)

Purpose

Relief of Allergic Rhinitis,
Acute Rhinitis, Chronic,Rhinitis and Inflammatory,Nasal Congestion

Use

First remove the protective cap, before first use, press several times until liquid squirts out, then insert the nozzle into the nostril, press firmly, pull the nozzle out of the nostril before releasing, then release, close the cap for protection.

Warnings

· For adults only.
· Use of this container by more than one person may spread infection.

Do not use: children, atrophic rhinitis, nasal dryness. Do not use when the character of this product changes.

When Using

When Using this product: avoid contact with eyes and mouth. If there is burning sensation, redness or
swelling at the site of application, the drug should be discontinued and the local drug should be washed off. Consult a physician if necessary.

Stop Use

Stop Using and ask a doctor if you have Hypertension, Coronary heart disease,
Hyperthyroidism or Allergic person.

Ask Doctor

Stop Using and ask a doctor if you have Hypertension, Coronary heart disease, Hyperthyroidism or Allergic person.

Keep Oot Of Reach Of Children

Keep out of reach of Children. In cacse of accidental ingestion, get medical help or contact a poison control center immediately.

Directions

No more than 4 times per day, with an interval of not less than 4 hours between each use, and not more than 7 days of continuous use.

Other information

If you are using other drugs, please consult your physician or pharmacist before using this product.
Shielded from light, sealed, stored in a cool place (not more than 20℃).

Inactive ingredients

Water, Glycosyl Trehalose, Schizophyllan, Citrus
Reticulata (Tangerine) Fruit Extract, Benzyl
Alcohol, Polysorbate 80, Sodium Citrate, Rhamnose,
Carboxymethyl Chitosan, Phenoxyethanol, Disodium Edta, Benzoic Acid